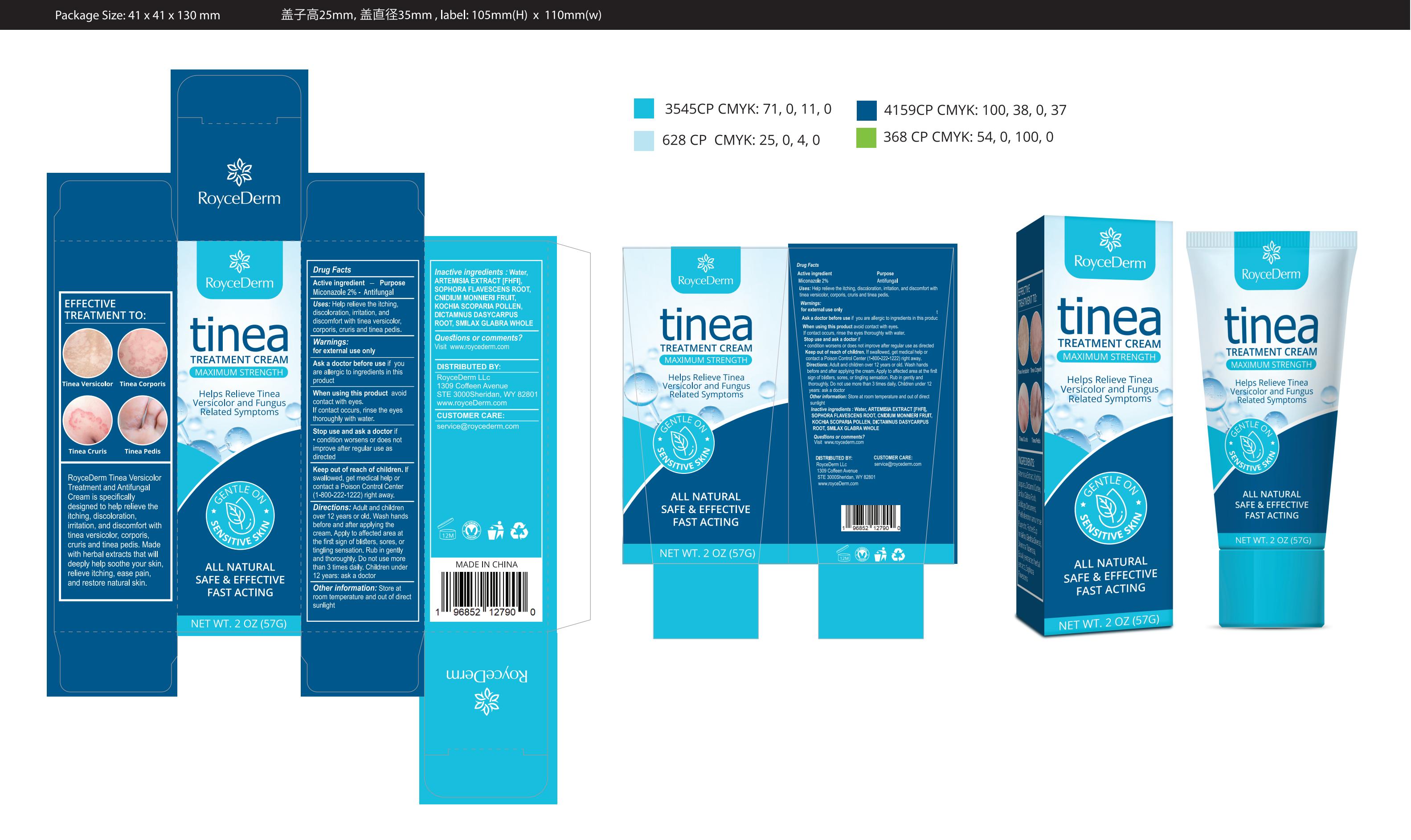 DRUG LABEL: Roycederm Tinea Treatment Cream
NDC: 84746-003 | Form: CREAM
Manufacturer: Shandong Yuyaotang Pharmaceutical Co., Ltd
Category: otc | Type: HUMAN OTC DRUG LABEL
Date: 20240919

ACTIVE INGREDIENTS: MICONAZOLE 2 g/100 g
INACTIVE INGREDIENTS: SMILAX GLABRA WHOLE; CNIDIUM MONNIERI FRUIT; WATER; WORMWOOD; SOPHORA FLAVESCENS ROOT; DICTAMNUS DASYCARPUS ROOT; BASSIA SCOPARIA POLLEN

84746-003

Active Ingredient

Miconazole 2%

Purpose

Antifungal

Use

Help relieve the itching.discoloration, irritation, anddiscomfort with tinea versicolorcorporis, cruris and tinea pedis.

Warnings

for external use only

Do not use

Children unde12 years: ask a doctor

When Using

avoidcontact with eyes.If contact occurs, rinse the eyesthoroughly with water.

Stop Use

if condition worsens or does notimprove after reqular use as directed

Ask Doctor

Ask a doctor before use if youare allergic to ingredients in thisproduct

Keep Oot Of Reach Of Children

Keep out of reach of children. lfswallowed, get medical help orcontact a Poison Control Cente(1-800-222-1222)right away.

Directions

Adult and childrenover 12 years or old. Wash handsbefore and after applying thecream. Apply to affected area atthe first sign of blisters, sores, ortingling sensation. Rub in gentlyand thoroughly. Do not use morethan 3 times daily. Children unde12 years: ask a doctor

Other information

Store atroom temperature and out of directsunlight

Inactive ingredients

Water,ARTEMISIA EXTRACT IFHFI],SOPHORA FLAVESCENS ROOT. CNIDIUM MONNIERI FRUITKOCHIA SCOPARIA POLLEN
DICTAMNUS DASYCARPUSROOT, SMILAX GLABRA WHOLE

Questions

Visit www.roycederm.com